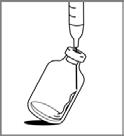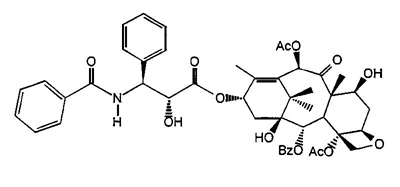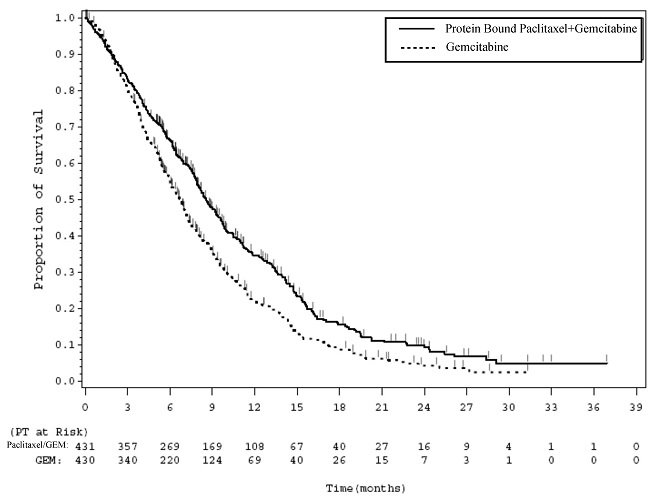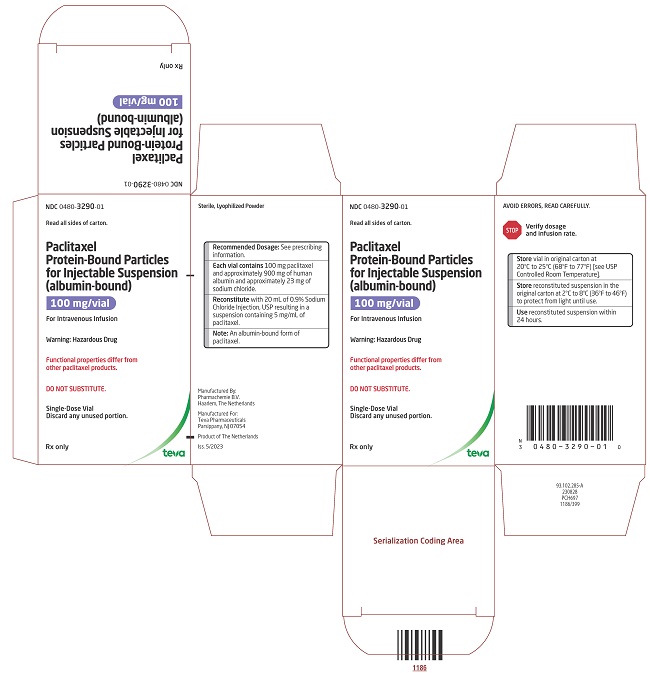 DRUG LABEL: Paclitaxel
NDC: 0480-3290 | Form: INJECTION, POWDER, LYOPHILIZED, FOR SUSPENSION
Manufacturer: Teva Pharmaceuticals, Inc.
Category: prescription | Type: HUMAN PRESCRIPTION DRUG LABEL
Date: 20231101

ACTIVE INGREDIENTS: PACLITAXEL 100 mg/20 mL
INACTIVE INGREDIENTS: ALBUMIN HUMAN; SODIUM CHLORIDE

HIGHLIGHTS OF PRESCRIBING INFORMATION

These highlights do not include all the information needed to use PACLITAXEL PROTEIN-BOUND PARTICLES FOR INJECTABLE SUSPENSION (ALBUMIN-BOUND) safely and effectively. See full prescribing information for PACLITAXEL PROTEIN-BOUND PARTICLES FOR INJECTABLE SUSPENSION (ALBUMIN-BOUND).
PACLITAXEL protein-bound particles for injectable suspension
(albumin-bound), for intravenous use
Initial U.S. Approval: 2005

WARNING: SEVERE MYELOSUPPRESSION

See full prescribing information for complete boxed warning.

- Do not administer Paclitaxel Protein-Bound Particles for Injectable Suspension (albumin-bound) therapy to patients with baseline neutrophil counts of less than 1,500 cells/mm^3. (4)
- Monitor for neutropenia, which may be severe and result in infection or sepsis. (5.1, 5.3)
- Perform frequent complete blood cell counts on all patients receiving Paclitaxel Protein-Bound Particles for Injectable Suspension (albumin-bound). (5.1, 5.3)

1 INDICATIONS AND USAGE

Paclitaxel Protein-Bound Particles for Injectable Suspension (albumin-bound) is a microtubule inhibitor indicated for the treatment of:

- Metastatic breast cancer, after failure of combination chemotherapy for metastatic disease or relapse within 6 months of adjuvant chemotherapy. Prior therapy should have included an anthracycline unless clinically contraindicated. (1.1)
- Locally advanced or metastatic non-small cell lung cancer (NSCLC), as first-line treatment in combination with carboplatin, in patients who are not candidates for curative surgery or radiation therapy. (1.2)
- Metastatic adenocarcinoma of the pancreas as first-line treatment, in combination with gemcitabine. (1.3)

2 DOSAGE AND ADMINISTRATION

- Do not substitute Paclitaxel Protein-Bound Particles for Injectable Suspension (albumin-bound) for other paclitaxel products. (2.1)
- Extravasation: Closely monitor the infusion site for extravasation and infiltration. (2.1)
- Metastatic Breast Cancer (MBC): Recommended dosage of Paclitaxel
  Protein-Bound Particles for Injectable Suspension (albumin-bound) is 260 mg/m^2 intravenously over 30 minutes every 3 weeks. (2.2)
- Non-Small Cell Lung Cancer (NSCLC): Recommended dosage of Paclitaxel Protein-Bound Particles for Injectable Suspension (albumin-bound) is 100 mg/m^2 intravenously over 30 minutes on Days 1, 8, and 15 of each 21-day cycle; administer carboplatin on Day 1 of each 21-day cycle immediately after Paclitaxel Protein-Bound Particles for Injectable Suspension (albumin-bound). (2.2)
- Adenocarcinoma of the Pancreas: Recommended dosage of Paclitaxel
  Protein-Bound Particles for Injectable Suspension (albumin-bound) is 125 mg/m^2 intravenously over 30 to 40 minutes on Days 1, 8, and 15 of each 28-day cycle; administer gemcitabine on Days 1, 8, and 15 of each 28-day cycle immediately after Paclitaxel Protein-Bound Particles for Injectable Suspension (albumin-bound). (2.4)
- Use in Patients with Hepatic Impairment: Paclitaxel Protein-Bound Particles for Injectable Suspension (albumin-bound) is not recommended for use in patients with AST > 10 x ULN; or bilirubin > 5 x ULN or with metastatic adenocarcinoma of the pancreas who have moderate to severe hepatic impairment. For MBC or NSCLC, reduce starting dose in patients with moderate to severe hepatic impairment. (2.5)
- Dose Reductions for Adverse Reactions: Dose reductions or discontinuation may be needed based on severe hematologic, neurologic, cutaneous, or gastrointestinal toxicities. (2.6)

3 DOSAGE FORMS AND STRENGTHS

For injectable suspension: white to yellow, lyophilized powder containing 100 mg of paclitaxel formulated as albumin-bound particles in single-dose vial for reconstitution. (3)

4 CONTRAINDICATIONS

- Neutrophil counts of <1,500 cells/mm^3. (4)
- Severe hypersensitivity reactions to protein bound paclitaxel. (4)

5 WARNINGS AND PRECAUTIONS

- Sensory neuropathy occurs frequently and may require dose reduction or treatment interruption. (5.2)
- Sepsis occurred in patients who received Paclitaxel Protein-Bound Particles for Injectable Suspension (albumin-bound); interrupt Paclitaxel Protein-Bound Particles for Injectable Suspension (albumin-bound) until sepsis resolves, and if neutropenia, until neutrophils are at least 1500 cells/mm^3, then resume treatment at reduced dose levels. (5.3)
- Pneumonitis occurred with the use of protein bound paclitaxel in combination with gemcitabine; permanently discontinue treatment with Paclitaxel Protein-Bound Particles for Injectable Suspension (albumin-bound) and gemcitabine. (5.4)
- Severe hypersensitivity reactions with fatal outcome have been reported. Do not rechallenge with this drug. (4, 5.5)
- Exposure and toxicity of paclitaxel can be increased in patients with hepatic impairment, consider dose reduction and closely monitor patients with hepatic impairment. (2.5, 5.6)
- Paclitaxel Protein-Bound Particles for Injectable Suspension (albumin-bound) contains albumin derived from human blood, which has a theoretical risk of viral transmission. (5.7)
- Paclitaxel Protein-Bound Particles for Injectable Suspension (albumin-bound) can cause fetal harm. Advise patients of potential risk to a fetus and to use effective contraception. (5.8, 8.1, 8.3)

6 ADVERSE REACTIONS

- The most common adverse reactions (≥20%) in metastatic breast cancer are alopecia, neutropenia, sensory neuropathy, abnormal ECG, fatigue/asthenia, myalgia/arthralgia, AST elevation, alkaline phosphatase elevation, anemia, nausea, infections, and diarrhea. (6.1)
- The most common adverse reactions (≥ 20%) in NSCLC are anemia, neutropenia, thrombocytopenia, alopecia, peripheral neuropathy, nausea, and fatigue. (6.1)
- The most common (≥ 20%) adverse reactions of protein bound paclitaxel in adenocarcinoma of the pancreas are neutropenia, fatigue, peripheral neuropathy, nausea, alopecia, peripheral edema, diarrhea, pyrexia, vomiting, decreased appetite, rash, and dehydration. (6.1)

To report SUSPECTED ADVERSE REACTIONS, contact Teva at 1-888-838-2872 or FDA at 1-800-FDA-1088 or www.fda.gov/medwatch.

7 DRUG INTERACTIONS

Use caution when concomitantly administering Paclitaxel Protein-Bound Particles for Injectable Suspension (albumin-bound) with inhibitors or inducers of either CYP2C8 or CYP3A4. (7)

8 USE IN SPECIFIC POPULATIONS

- Lactation: Advise not to breastfeed. (8.2)

FULL PRESCRIBING INFORMATION

WARNING: SEVERE MYELOSUPPRESSION

- Do not administer Paclitaxel Protein-Bound Particles for Injectable Suspension (albumin-bound) therapy to patients who have baseline neutrophil counts of less than 1,500 cells/mm^3. [see Contraindications (4)].
- Monitor for neutropenia, which may be severe and result in infection or sepsis, [see Warnings and Precautions (5.1, 5.3)].
- Perform frequent complete blood cell counts on all patients receiving Paclitaxel Protein-Bound Particles for Injectable Suspension (albumin-bound) [see Contraindications (4), Warnings and Precautions (5.1, 5.3)].

1 INDICATIONS AND USAGE

1.1 Metastatic Breast Cancer

Paclitaxel Protein-Bound Particles for Injectable Suspension (albumin-bound) is indicated for the treatment of breast cancer after failure of combination chemotherapy for metastatic disease or relapse within 6 months of adjuvant chemotherapy. Prior therapy should have included an anthracycline unless clinically contraindicated.

1.2 Non-Small Cell Lung Cancer

Paclitaxel Protein-Bound Particles for Injectable Suspension (albumin-bound) is indicated for the first-line treatment of locally advanced or metastatic non-small cell lung cancer, in combination with carboplatin, in patients who are not candidates for curative surgery or radiation therapy.

1.3 Adenocarcinoma of the Pancreas

Paclitaxel Protein-Bound Particles for Injectable Suspension (albumin-bound) is indicated for the first-line treatment of patients with metastatic adenocarcinoma of the pancreas, in combination with gemcitabine.

2 DOSAGE AND ADMINISTRATION

2.1 Important Administration Instructions

DO NOT SUBSTITUTE FOR OR WITH OTHER PACLITAXEL FORMULATIONS. Paclitaxel Protein-Bound Particles for Injectable Suspension (albumin-bound) has different dosage and administration instructions from other paclitaxel products.

Closely monitor the infusion site for extravasation or drug infiltration during administration. Limiting the infusion of Paclitaxel Protein-Bound Particles for Injectable Suspension (albumin-bound) to 30 minutes may reduce the risk of infusion-related reactions [see Adverse Reactions (6.2)].

Consider premedication in patients who have had prior hypersensitivity reactions to Paclitaxel Protein-Bound Particles for Injectable Suspension (albumin-bound). Do not re-challenge patients who experience a severe hypersensitivity reaction to Paclitaxel Protein-Bound Particles for Injectable Suspension (albumin-bound) [see Contraindications (4) and Warnings and Precautions (5.5)].

2.2 Recommended Dosage for Metastatic Breast Cancer

After failure of combination chemotherapy for metastatic breast cancer or relapse within 6 months of adjuvant chemotherapy, the recommended regimen for Paclitaxel Protein-Bound Particles for Injectable Suspension (albumin-bound) is 260 mg/m^2 administered intravenously over 30 minutes every 3 weeks.

2.3 Recommended Dosage for Non-Small Cell Lung Cancer

The recommended dose of Paclitaxel Protein-Bound Particles for Injectable Suspension (albumin-bound) is 100 mg/m^2 administered as an intravenous infusion over 30 minutes on Days 1, 8, and 15 of each 21-day cycle. Administer carboplatin on Day 1 of each 21-day cycle immediately after Paclitaxel Protein-Bound Particles for Injectable Suspension (albumin-bound) [see Clinical Studies (14.2)].

2.4 Recommended Dosage for Adenocarcinoma of the Pancreas

The recommended dose of Paclitaxel Protein-Bound Particles for Injectable Suspension (albumin-bound) is 125 mg/m^2 administered as an intravenous infusion over 30 to 40 minutes on Days 1, 8, and 15 of each 28-day cycle. Administer gemcitabine immediately after Paclitaxel Protein-Bound Particles for Injectable Suspension (albumin-bound) on Days 1, 8, and 15 of each 28-day cycle [see Clinical Studies (14.3)].

2.5 Dosage Modifications for Hepatic Impairment

For patients with moderate or severe hepatic impairment, reduce the starting dose of Paclitaxel Protein-Bound Particles for Injectable Suspension (albumin-bound) as shown in Table 1.

Table 1: Recommendations for Starting Dose in Patients with Moderate and Severe Hepatic Impairment
 | AST Levels |  | Bilirubin; Levels | Paclitaxel Protein-Bound Particles for Injectable Suspension (albumin-bound) Dosea
 | AST Levels |  | Bilirubin; Levels | MBC | NSCLCc | Adenocarcinoma of Pancreasc
Moderate | <10 x ULN | AND | >1.5 to ≤3 x ULN | 200 mg/m2b | 80 mg/m2b | not recommended
Severe | <10 x ULN | AND | >3 to ≤5 x ULN | 200 mg/m2b | 80 mg/m2b | not recommended
Severe | >10 x ULN | OR | >5 x ULN | not recommended | not recommended | not recommended
AST = Aspartate Aminotransferase; MBC = Metastatic Breast Cancer; NSCLC = Non-Small Cell Lung Cancer; ULN = Upper limit of normal.
a Dosage recommendations are for the first course of therapy. The need for further dose adjustments in subsequent courses should be based on individual tolerance.
b A dose increase to 260 mg/m^2 for patients with metastatic breast cancer or 100 mg/m^2 for patients with non-small cell lung cancer in subsequent courses should be considered if the patient tolerates the reduced dose for two cycles.
c Patients with bilirubin levels above the upper limit of normal were excluded from clinical trials for pancreatic or lung cancer.

2.6 Dosage Modifications for Adverse Reactions

Metastatic Breast Cancer

Patients who experience severe neutropenia (neutrophils less than 500 cells/mm^3 for a week or longer) or severe sensory neuropathy during Paclitaxel Protein-Bound Particles for Injectable Suspension (albumin-bound) therapy should have dosage reduced to 220 mg/m^2 for subsequent courses of Paclitaxel Protein-Bound Particles for Injectable Suspension (albumin-bound). For recurrence of severe neutropenia or severe sensory neuropathy, additional dose reduction should be made to 180 mg/m^2. For Grade 3 sensory neuropathy hold treatment until resolution to Grade 1 or 2, followed by a dose reduction for all subsequent courses of Paclitaxel Protein-Bound Particles for Injectable Suspension (albumin-bound) [see Contraindications (4), Warnings and Precautions (5.1, 5.2) and Adverse Reactions (6.1)].

Non-Small Cell Lung Cancer

- Do not administer Paclitaxel Protein-Bound Particles for Injectable Suspension (albumin-bound) on Day 1 of a cycle until absolute neutrophil count (ANC) is at least 1,500 cells/mm^3 and platelet count is at least 100,000 cells/mm^3 [see Contraindications (4), Warnings and Precautions (5.1) and Adverse Reactions (6.1)].
- In patients who develop severe neutropenia or thrombocytopenia withhold treatment until counts recover to an absolute neutrophil count of at least 1,500 cells/mm^3 and platelet count of at least 100,000 cells/mm^3 on Day 1 or to an absolute neutrophil count of at least 500 cells/mm^3 and platelet count of at least
  50,000 cells/mm^3 on Days 8 or 15 of the cycle. Upon resumption of dosing, permanently reduce Paclitaxel Protein-Bound Particles for Injectable Suspension (albumin-bound) and carboplatin doses as outlined in Table 2.
- Withhold Paclitaxel Protein-Bound Particles for Injectable Suspension (albumin-bound) for Grade 3-4 peripheral neuropathy. Resume Paclitaxel Protein-Bound Particles for Injectable Suspension (albumin-bound) and carboplatin at reduced doses (see Table 2) when peripheral neuropathy improves to Grade 1 or completely resolves [see Warnings and Precautions (5.2) and Adverse Reactions (6.1)].

Table 2: Permanent Dose Reductions for Hematologic and Neurologic Adverse Reactions in NSCLC
Adverse Reaction | Occurrence | Weekly; Paclitaxel Protein-Bound Particles for Injectable Suspension (albumin-bound) Dose (mg/m^2) | Every 3-Week; Carboplatin Dose; (AUC mg•min/mL)
Neutropenic Fever (ANC less than 500/mm^3 with fever >38°C); OR; Delay of next cycle by more than 7 days for ANC less than 1500/mm^3; OR; ANC less than 500/mm^3 for more than 7 days | First | 75 | 4.5
Neutropenic Fever (ANC less than 500/mm^3 with fever >38°C); OR; Delay of next cycle by more than 7 days for ANC less than 1500/mm^3; OR; ANC less than 500/mm^3 for more than 7 days | Second | 50 | 3
Neutropenic Fever (ANC less than 500/mm^3 with fever >38°C); OR; Delay of next cycle by more than 7 days for ANC less than 1500/mm^3; OR; ANC less than 500/mm^3 for more than 7 days | Third | Discontinue Treatment
Platelet count less than 50,000/mm^3 | First | 75 | 4.5
Platelet count less than 50,000/mm^3 | Second | Discontinue Treatment
Severe sensory Neuropathy – Grade 3 or 4 | First | 75 | 4.5
Severe sensory Neuropathy – Grade 3 or 4 | Second | 50 | 3
Severe sensory Neuropathy – Grade 3 or 4 | Third | Discontinue Treatment

Adenocarcinoma of the Pancreas

Dose level reductions for patients with adenocarcinoma of the pancreas, as referenced in Tables 4 and 5, are provided in Table 3.

Table 3: Dose Level Reductions for Patients with Adenocarcinoma of the Pancreas
Dose Level | Paclitaxel Protein-Bound Particles for Injectable Suspension (albumin-bound) (mg/m^2) | Gemcitabine (mg/m^2)
Full dose | 125 | 1,000
1st dose reduction | 100 | 800
2nd dose reduction | 75 | 600
If additional dose reduction required | Discontinue | Discontinue

Recommended dose modifications for neutropenia and thrombocytopenia for patients with adenocarcinoma of the pancreas are provided in Table 4.

Table 4: Dose Recommendation and Modifications for Neutropenia and/or Thrombocytopenia at the Start of a Cycle or within a Cycle for Patients with Adenocarcinoma of the Pancreas
Cycle; Day | ANC (cells/mm^3) |  | Platelet count (cells/mm^3) |  | Paclitaxel Protein-Bound Particles for Injectable Suspension (albumin-bound) / Gemcitabine
Day 1 | < 1,500 | OR | < 100,000 |  | Delay doses until recovery
Day 8 | 500 to < 1,000 | OR | 50,000 to < 75,000 |  | Reduce 1 dose level
 | < 500 | OR | < 50,000 |  | Withhold doses
Day 15: If Day 8 doses were reduced or given without modification:
 | 500 to < 1,000 | OR | 50,000 to < 75,000 |  | Reduce 1 dose level from Day 8
 | < 500 | OR | < 50,000 |  | Withhold doses
Day 15: If Day 8 doses were withheld:
 | ≥ 1,000 | OR | ≥ 75,000 | Reduce 1 dose level from Day 1
 | 500 to < 1,000 | OR | 50,000 to < 75,000 | Reduce 2 dose levels from Day 1
 | < 500 | OR | < 50,000 | Withhold doses
ANC = Absolute Neutrophil Count

Recommended dose modifications for other adverse reactions in patients with adenocarcinoma of the pancreas are provided in Table 5.

Table 5: Dose Modifications for Other Adverse Reactions in Patients with Adenocarcinoma of the Pancreas
Adverse Reaction | Paclitaxel Protein-Bound Particles for Injectable Suspension (albumin-bound) | Gemcitabine
Febrile Neutropenia:; Grade 3 or 4 | Withhold until fever resolves and ANC ≥ 1,500; resume at next lower dose level
Peripheral Neuropathy:; Grade 3 or 4 | Withhold until improves to ≤ Grade 1;; resume at next lower dose level | No dose reduction
Cutaneous Toxicity:; Grade 2 or 3 | Reduce to next lower dose level; discontinue treatment if toxicity persists
Gastrointestinal Toxicity:; Grade 3 mucositis or diarrhea | Withhold until improves to ≤ Grade 1;; resume at next lower dose level

2.7 Preparation for Intravenous Administration

Paclitaxel Protein-Bound Particles for Injectable Suspension (albumin-bound) is a hazardous drug. Follow applicable special handling and disposal procedures.^1 The use of gloves is recommended. If Paclitaxel Protein-Bound Particles for Injectable Suspension (albumin-bound) (lyophilized cake or reconstituted suspension) contacts the skin, wash the skin immediately and thoroughly with soap and water. Following topical exposure to paclitaxel, events may include tingling, burning, and redness. If Paclitaxel Protein-Bound Particles for Injectable Suspension (albumin-bound) contacts mucous membranes, the membranes should be flushed thoroughly with water.

Paclitaxel Protein-Bound Particles for Injectable Suspension (albumin-bound) is supplied as a sterile lyophilized powder for reconstitution before use.

Read the entire preparation instructions prior to reconstitution.

1. Aseptically, reconstitute each vial by injecting 20 mL of 0.9% Sodium Chloride Injection, USP.

2. Slowly inject the 20 mL of 0.9% Sodium Chloride Injection, USP, over a minimum of 1 minute, using the sterile syringe to direct the solution flow onto the INSIDE WALL OF THE VIAL.

3. DO NOT INJECT the 0.9% Sodium Chloride Injection, USP, directly onto the lyophilized cake as this will result in foaming.

4. Once the injection is complete, allow the vial to sit for a minimum of 5 minutes to ensure proper wetting of the lyophilized cake/powder.

5. Gently swirl and/or invert the vial slowly for at least 2 minutes until complete dissolution of any cake/powder occurs. Avoid generation of foam.

6. If foaming or clumping occurs, stand solution for at least 15 minutes until foam subsides.

Each mL of the reconstituted formulation will contain 5 mg/mL paclitaxel.

The reconstituted suspension should be milky and homogenous without visible particulates. If particulates or settling are visible, the vial should be gently inverted again to ensure complete resuspension prior to use. Discard the reconstituted suspension if precipitates are observed. Discard any unused portion.

Calculate the exact total dosing volume of 5 mg/mL suspension required for the patient and slowly withdraw the dosing volume of the reconstituted suspension from the vial(s) into a syringe: Dosing volume (mL)=Total dose (mg)/5 (mg/mL).

Inject the appropriate amount of reconstituted Paclitaxel Protein-Bound Particles for Injectable Suspension (albumin-bound) into an empty, sterile intravenous bag [plasticized polyvinyl chloride (PVC) containers, PVC or non-PVC type intravenous bag]. The use of specialized DEHP-free solution containers or administration sets is not necessary to prepare or administer Paclitaxel Protein-Bound Particles for Injectable Suspension (albumin-bound) infusions. The use of medical devices containing silicone oil as a lubricant (i.e., syringes and intravenous bags) to reconstitute and administer Paclitaxel Protein-Bound Particles for Injectable Suspension (albumin-bound) may result in the formation of proteinaceous strands.

Visually inspect the reconstituted Paclitaxel Protein-Bound Particles for Injectable Suspension (albumin-bound) suspension in the intravenous bag prior to administration. Discard the reconstituted suspension if proteinaceous strands, particulate matter, or discoloration are observed.

2.8 Stability

Stability of Reconstituted Suspension in the Vial

Reconstituted Paclitaxel Protein-Bound Particles for Injectable Suspension (albumin-bound) in the vial should be used immediately, but may be refrigerated at 2°C to 8°C (36°F to 46°F) for a maximum of 24 hours if necessary. If not used immediately, each vial of reconstituted suspension should be replaced in the original carton to protect it from light. Discard any unused portion.

Stability of Reconstituted Suspension in the Infusion Bag

The suspension for infusion when prepared as recommended in an infusion bag should be used immediately, but may be refrigerated at 2°C to 8°C (36°F to 46°F) and protected from light for a maximum of 24 hours.

The total combined refrigerated storage time of reconstituted Paclitaxel Protein-Bound Particles for Injectable Suspension (albumin-bound) in the vial and in the infusion bag is 24 hours. This may be followed by storage in the infusion bag at ambient temperature (approximately 25°C) and lighting conditions for a maximum of 4 hours.

Discard any unused portion.

3 DOSAGE FORMS AND STRENGTHS

For injectable suspension: white to yellow lyophilized powder containing 100 mg of paclitaxel formulated as albumin-bound particles in a single-dose vial for reconstitution.

4 CONTRAINDICATIONS

Paclitaxel Protein-Bound Particles for Injectable Suspension (albumin-bound) is contraindicated in patients with:

- Baseline neutrophil counts of <1,500 cells/mm^3 [see Warnings and Precautions (5.1)]
- A history of severe hypersensitivity reactions to protein bound paclitaxel [see Warnings and Precautions (5.5)]

5 WARNINGS AND PRECAUTIONS

5.1 Severe Myelosuppression

Severe myelosuppression (primarily neutropenia) is dose-dependent and a dose-limiting toxicity of protein bound paclitaxel. In clinical studies, Grade 3-4 neutropenia occurred in 34% of patients with metastatic breast cancer (MBC), 47% of patients with non-small cell lung cancer (NSCLC), and 38% of patients with pancreatic cancer.

Monitor for severe neutropenia and thrombocytopenia by performing complete blood cell counts frequently, including prior to dosing on Day 1 (for MBC) and Days 1, 8, and 15 (for NSCLC and for pancreatic cancer). Do not administer Paclitaxel Protein-Bound Particles for Injectable Suspension (albumin-bound) to patients with baseline absolute neutrophil counts (ANC) of less than 1,500 cells/mm^3 [see Contraindications (4)].

In the case of severe neutropenia (<500 cells/mm^3 for seven days or more) during a course of Paclitaxel Protein-Bound Particles for Injectable Suspension (albumin-bound) therapy, reduce the dose of Paclitaxel Protein-Bound Particles for Injectable Suspension (albumin-bound) in subsequent courses in patients with either MBC or NSCLC.

In patients with MBC, resume treatment with every-3-week cycles of Paclitaxel Protein-Bound Particles for Injectable Suspension (albumin-bound) after ANC recovers to a level >1,500 cells/mm^3 and platelets recover to a level >100,000 cells/mm^3. In patients with NSCLC, resume treatment if recommended at permanently reduced doses for both weekly protein-bound paclitaxel for Injectable Suspension (albumin-bound) and every-3-week carboplatin after ANC recovers to at least 1,500 cells/mm^3 and platelet count of at least 100,000 cells/mm^3 on Day 1 or to an ANC of at least 500 cells/mm^3 and platelet count of at least 50,000 cells/mm^3 on Days 8 or 15 of the cycle [see Dosage and Administration (2.6)].

In patients with adenocarcinoma of the pancreas, withhold Paclitaxel Protein-Bound Particles for Injectable Suspension (albumin-bound) and gemcitabine if the ANC is less than 500 cells/mm^3 or platelets are less than 50,000 cells/mm^3 and delay initiation of the next cycle if the ANC is less than 1,500 cells/mm^3 or platelet count is less than 100,000 cells/mm^3 on Day 1 of the cycle. Resume treatment with appropriate dose reduction if recommended [see Dosage and Administration (2.6)].

5.2 Severe Neuropathy

Sensory neuropathy is dose- and schedule-dependent [see Adverse Reactions (6.1)]. If ≥ Grade 3 sensory neuropathy develops, withhold Paclitaxel Protein-Bound Particles for Injectable Suspension (albumin-bound) treatment until resolution to Grade 1 or 2 for metastatic breast cancer or until resolution to ≤ Grade 1 for NSCLC and pancreatic cancer followed by a dose reduction for all subsequent courses of Paclitaxel Protein-Bound Particles for Injectable Suspension (albumin-bound) [see Dosage and Administration (2.6)].

5.3 Sepsis

Sepsis occurred in 5% of patients with or without neutropenia who received Paclitaxel Protein-Bound Particles for Injectable Suspension (albumin-bound) in combination with gemcitabine. Biliary obstruction or presence of biliary stent were risk factors for severe or fatal sepsis.

If a patient becomes febrile (regardless of ANC) initiate treatment with broad spectrum antibiotics. For febrile neutropenia, interrupt Paclitaxel Protein-Bound Particles for Injectable Suspension (albumin-bound) until fever resolves and ANC ≥1,500, then resume treatment at reduced dose levels [see Dosage and Administration (2.6)].

5.4 Pneumonitis

Pneumonitis, including some cases that were fatal, occurred in 4% of patients receiving protein bound paclitaxel in combination with gemcitabine.

Monitor patients for signs and symptoms of pneumonitis and interrupt Paclitaxel Protein-Bound Particles for Injectable Suspension (albumin-bound) and gemcitabine during evaluation of suspected pneumonitis. After ruling out infectious etiology and upon making a diagnosis of pneumonitis, permanently discontinue treatment with Paclitaxel Protein-Bound Particles for Injectable Suspension (albumin-bound) and gemcitabine.

5.5 Severe Hypersensitivity

Severe and sometimes fatal hypersensitivity reactions, including anaphylactic reactions, have been reported. Do not rechallenge patients who experience a severe hypersensitivity reaction to protein bound paclitaxel with this drug [see Contraindications (4)].

Cross-hypersensitivity between protein bound paclitaxel and other taxane products has been reported and may include severe reactions such as anaphylaxis. Closely monitor patients with a previous history of hypersensitivity to other taxanes during initiation of Paclitaxel Protein-Bound Particles for Injectable Suspension (albumin-bound) therapy.

5.6 Use in Patients with Hepatic Impairment

The exposure and toxicity of paclitaxel can be increased in patients with hepatic impairment. Closely monitor patients with hepatic impairment for severe myelosuppression.

Paclitaxel Protein-Bound Particles for Injectable Suspension (albumin-bound) is not recommended in patients who have total bilirubin >5 x ULN or AST >10 x ULN. In addition, protein-bound paclitaxel for Injectable Suspension (albumin-bound) is not recommended in patients with metastatic adenocarcinoma of the pancreas who have moderate to severe hepatic impairment (total bilirubin >1.5 x ULN and AST ≤10 x ULN). Reduce the starting dose for patients with moderate or severe hepatic impairment [see Dosage and Administration (2.5), Use in Specific Populations (8.7), Clinical Pharmacology (12.3)].

5.7 Albumin (Human)

Paclitaxel Protein-Bound Particles for Injectable Suspension (albumin-bound) contains albumin (human), a derivative of human blood. Based on effective donor screening and product manufacturing processes, it carries a remote risk for transmission of viral diseases. A theoretical risk for transmission of Creutzfeldt-Jakob Disease (CJD) also is considered extremely remote. No cases of transmission of viral diseases or CJD have ever been identified for albumin.

5.8 Embryo-Fetal Toxicity

Based on mechanism of action and findings in animals, Paclitaxel Protein-Bound Particles for Injectable Suspension (albumin-bound) can cause fetal harm when administered to a pregnant woman. In animal reproduction studies, administration of protein bound paclitaxel to rats during pregnancy at doses lower than the maximum recommended human dose, based on body surface area, caused embryo-fetal toxicities, including intrauterine mortality, increased resorptions, reduced numbers of live fetuses, and malformations.

Advise females of reproductive potential of the potential risk to a fetus. Advise females of reproductive potential to use effective contraception and avoid becoming pregnant during treatment with Paclitaxel Protein-Bound Particles for Injectable Suspension (albumin-bound) and for at least six months after the last dose [see Use in Specific Populations (8.1, 8.3), Clinical Pharmacology (12.1)].

Based on findings from genetic toxicity and animal reproduction studies, advise male patients with female partners of reproductive potential to use effective contraception and avoid fathering a child during treatment with Paclitaxel Protein-Bound Particles for Injectable Suspension (albumin-bound) and for at least three months after the last dose [see Use in Specific Populations (8.1, 8.3), Nonclinical Toxicology (13.1)].

6 ADVERSE REACTIONS

The following adverse reactions are described elsewhere in the labeling:

- Severe Myelosuppression [see Warnings and Precautions (5.1)]
- Severe Neuropathy [see Warnings and Precautions (5.2)]
- Sepsis [see Warnings and Precautions (5.3)]
- Pneumonitis [see Warnings and Precautions (5.4)]
- Severe Hypersensitivity [see Warnings and Precautions (5.5)]

6.1 Clinical Trials Experience

Because clinical trials are conducted under widely varying conditions, adverse reaction rates observed in the clinical trials of a drug cannot be directly compared to rates in the clinical trials of another drug and may not reflect the rates observed in practice.

The most common adverse reactions (≥20%) with single-agent use of protein bound paclitaxel in metastatic breast cancer are alopecia, neutropenia, sensory neuropathy, abnormal ECG, fatigue/asthenia, myalgia/arthralgia, AST elevation, alkaline phosphatase elevation, anemia, nausea, infections, and diarrhea [see Adverse Reactions (6.1)].

The most common adverse reactions (≥ 20%) of protein bound paclitaxel in combination with carboplatin for non-small cell lung cancer are anemia, neutropenia, thrombocytopenia, alopecia, peripheral neuropathy, nausea, and fatigue [see Adverse Reactions (6.1)]. The most common serious adverse reactions of protein bound paclitaxel in combination with carboplatin for non-small cell lung cancer are anemia (4%) and pneumonia (3%). The most common adverse reactions resulting in permanent discontinuation of protein bound paclitaxel are neutropenia (3%), thrombocytopenia (3%), and peripheral neuropathy (1%). The most common adverse reactions resulting in dose reduction of protein bound paclitaxel are neutropenia (24%), thrombocytopenia (13%), and anemia (6%). The most common adverse reactions leading to withholding or delay in protein bound paclitaxel dosing are neutropenia (41%), thrombocytopenia (30%), and anemia (16%).

In a randomized open-label trial of protein bound paclitaxel in combination with gemcitabine for pancreatic adenocarcinoma [see Clinical Studies (14.3)], the most common (≥ 20%) selected (with a ≥ 5% higher incidence) adverse reactions of protein bound paclitaxel are neutropenia, fatigue, peripheral neuropathy, nausea, alopecia, peripheral edema, diarrhea, pyrexia, vomiting, decreased appetite, rash, and dehydration [see Adverse Reactions (6.1)]. The most common serious adverse reactions of protein bound paclitaxel (with a ≥ 1% higher incidence) are pyrexia (6%), dehydration (5%), pneumonia (4%), and vomiting (4%). The most common adverse reactions resulting in permanent discontinuation of protein bound paclitaxel are peripheral neuropathy (8%), fatigue (4%), and thrombocytopenia (2%). The most common adverse reactions resulting in dose reduction of protein bound paclitaxel are neutropenia (10%) and peripheral neuropathy (6%). The most common adverse reactions leading to withholding or delay in protein bound paclitaxel dosing are neutropenia (16%), thrombocytopenia (12%), fatigue (8%), peripheral neuropathy (15%), anemia (5%), and diarrhea (5%).

Metastatic Breast Cancer

Table 6 shows the frequency of important adverse reactions in the randomized comparative trial for the patients who received either single-agent protein bound paclitaxel or paclitaxel injection for the treatment of metastatic breast cancer.

Table 6: Adverse Reactions in the Randomized Metastatic Breast Cancer Study on an Every-3-Weeks Schedule
 | Percent of Patients
 | Protein Bound Paclitaxel; 260 mg/m^2 over 30 min; (n=229) | Paclitaxel Injection; 175 mg/m^2 over 3 ha; (n=225)
Bone Marrow
Neutropenia
<2.0 x 10^9/L | 80 | 82
<0.5 x 10^9/L | 9 | 22
Thrombocytopenia
<100 x 10^9/L | 2 | 3
<50 x 10^9/L | <1 | <1
Anemia
<11 g/dL | 33 | 25
<8 g/dL | 1 | <1
Infections | 24 | 20
Febrile Neutropenia | 2 | 1
Neutropenic Sepsis | <1 | <1
Bleeding | 2 | 2
Hypersensitivity Reactionb
All | 4 | 12
Severec | 0 | 2
Cardiovascular
Vital Sign Changes During Administration
Bradycardia | <1 | <1
Hypotension | 5 | 5
Severe Cardiovascular Eventsc | 3 | 4
Abnormal ECG
All Patients | 60 | 52
Patients with Normal Baseline | 35 | 30
Respiratory
Cough | 7 | 6
Dyspnea | 12 | 9
Sensory Neuropathy
Any Symptoms | 71 | 56
Severe Symptomsc | 10 | 2
Myalgia / Arthralgia
Any Symptoms | 44 | 49
Severe Symptomsc | 8 | 4
Asthenia
Any Symptoms | 47 | 39
Severe Symptomsc | 8 | 3
Fluid Retention/Edema
Any Symptoms | 10 | 8
Severe Symptomsc | 0 | <1
Gastrointestinal
Nausea
Any Symptoms | 30 | 22
Severe Symptomsc | 3 | <1
Vomiting
Any Symptoms | 18 | 10
Severe Symptomsc | 4 | 1
Diarrhea
Any Symptoms | 27 | 15
Severe Symptomsc | <1 | 1
Mucositis
Any Symptoms | 7 | 6
Severe Symptomsc | <1 | 0
Alopecia | 90 | 94
Hepatic (Patients with Normal Baseline)
Bilirubin Elevations | 7 | 7
Alkaline Phosphatase Elevations | 36 | 31
AST (SGOT) Elevations | 39 | 32
Injection Site Reaction | <1 | 1
a Paclitaxel injection patients received premedication.
b Includes treatment-related events related to hypersensitivity (e.g., flushing, dyspnea, chest pain, hypotension) that began on a day of dosing.
c Severe events are defined as at least Grade 3 toxicity.

Other Adverse Reactions

Hematologic Disorders

Neutropenia was dose dependent and reversible. Among patients with metastatic breast cancer in the randomized trial, neutrophil counts declined below 500 cells/mm^3 (Grade 4) in 9% of the patients treated with a dose of 260 mg/m^2 compared to 22% in patients receiving paclitaxel injection at a dose of 175 mg/m^2. Pancytopenia has been observed in clinical trials.

Infections

Infectious episodes were reported in 24% of the patients treated with protein bound paclitaxel. Oral candidiasis, respiratory tract infections and pneumonia were the most frequently reported infectious complications.

Hypersensitivity Reactions (HSRs)

Grade 1 or 2 HSRs occurred on the day of protein bound paclitaxel administration and consisted of dyspnea (1%) and flushing, hypotension, chest pain, and arrhythmia (all <1%). The use of Paclitaxel Protein-Bound Particles for Injectable Suspension (albumin-bound) in patients previously exhibiting hypersensitivity to paclitaxel injection or human albumin has not been studied.

Cardiovascular

Hypotension, during the 30-minute infusion, occurred in 5% of patients. Bradycardia, during the 30-minute infusion, occurred in <1% of patients. These vital sign changes most often caused no symptoms and required neither specific therapy nor treatment discontinuation.

Severe cardiovascular events possibly related to single-agent protein bound paclitaxel occurred in approximately 3% of patients. These events included cardiac ischemia/infarction, chest pain, cardiac arrest, supraventricular tachycardia, edema, thrombosis, pulmonary thromboembolism, pulmonary emboli, and hypertension. Cases of cerebrovascular attacks (strokes) and transient ischemic attacks have been reported.

Electrocardiogram (ECG) abnormalities were common among patients at baseline. ECG abnormalities on study did not usually result in symptoms, were not dose-limiting, and required no intervention. ECG abnormalities were noted in 60% of patients. Among patients with a normal ECG prior to study entry, 35% of all patients developed an abnormal tracing while on study. The most frequently reported ECG modifications were
non-specific repolarization abnormalities, sinus bradycardia, and sinus tachycardia.

Respiratory

Dyspnea (12%), cough (7%), and pneumothorax (<1%) were reported after treatment with protein bound paclitaxel.

Neurologic

The frequency and severity of sensory neuropathy increased with cumulative dose. Sensory neuropathy was the cause of protein bound paclitaxel discontinuation in 7/229 (3%) patients. Twenty-four patients (10%) treated with protein bound paclitaxel developed Grade 3 peripheral neuropathy; of these patients, 14 had documented improvement after a median of 22 days; 10 patients resumed treatment at a reduced dose of protein bound paclitaxel and 2 discontinued due to peripheral neuropathy. Of the 10 patients without documented improvement, 4 discontinued the study due to peripheral neuropathy.

No Grade 4 sensory neuropathies were reported. Only one incident of motor neuropathy (Grade 2) was observed in either arm of the controlled trial.

Vision Disorders

Ocular/visual disturbances occurred in 13% of all patients (n=366) treated with protein bound paclitaxel and
1% were severe. The severe cases (keratitis and blurred vision) were reported in patients who received higher doses than those recommended (300 or 375 mg/m^2). These effects generally have been reversible.

Arthralgia/Myalgia

The symptoms were usually transient, occurred two or three days after protein bound paclitaxel administration, and resolved within a few days.

Hepatic

Grade 3 or 4 elevations in GGT were reported for 14% of patients treated with protein bound paclitaxel and 10% of patients treated with paclitaxel injection in the randomized trial.

Renal

Overall 11% of patients experienced creatinine elevation, 1% severe. No discontinuations, dose reductions, or dose delays were caused by renal toxicities.

Other Clinical Events

Nail changes (changes in pigmentation or discoloration of nail bed) have been reported. Edema occurred in 10% of patients; no patients had severe edema. Dehydration and pyrexia were also reported.

Non-Small Cell Lung Cancer

Adverse reactions were assessed in 514 protein bound paclitaxel/carboplatin-treated patients and 524 paclitaxel injection/carboplatin-treated patients receiving first-line systemic treatment for locally advanced (stage IIIB) or metastatic (IV) non-small cell lung cancer (NSCLC) in a multicenter, randomized, open-label trial. Protein bound paclitaxel was administered as an intravenous infusion over 30 minutes at a dose of 100 mg/m^2 on Days 1, 8, and 15 of each 21-day cycle. Paclitaxel injection was administered as an intravenous infusion over 3 hours at a dose of 200 mg/m^2, following premedication. In both treatment arms carboplatin at a dose of AUC =
6 mg•min/mL was administered intravenously on Day 1 of each 21-day cycle after completion of protein bound paclitaxel/paclitaxel infusion.

The differences in paclitaxel dose and schedule between the two arms limit direct comparison of dose- and schedule-dependent adverse reactions. Among patients evaluable for adverse reactions, the median age was
60 years, 75% were men, 81% were White, 49% had adenocarcinoma, 43% had squamous cell lung cancer, 76% were ECOG PS 1. Patients in both treatment arms received a median of 6 cycles of treatment.

The following common (≥ 10% incidence) adverse reactions were observed at a similar incidence in protein bound paclitaxel plus carboplatin-treated and paclitaxel injection plus carboplatin-treated patients: alopecia 56%, nausea 27%, fatigue 25%, decreased appetite 17%, asthenia 16%, constipation 16%, diarrhea 15%, vomiting 12%, dyspnea 12%, and rash 10% (incidence rates are for the protein bound paclitaxel plus carboplatin treatment group).

Table 7 provides the frequency and severity of laboratory-detected abnormalities which occurred with a difference of ≥ 5% for all grades (1-4) or ≥ 2% for Grade 3-4 toxicity between protein bound paclitaxel plus carboplatin-treated patients or paclitaxel injection plus carboplatin-treated patients.

Table 7: Selected Hematologic Laboratory-Detected Abnormalities with a Difference of ≥ 5% for grades (1-4) or ≥ 2% for Grade 3-4 Toxicity Between Treatment Groups
 | Protein Bound Paclitaxel (100 mg/m^2 weekly) plus carboplatin |  | Paclitaxel Injection (200 mg/m^2 every 3 weeks) plus carboplatin
 | Grades 1-4 (%) | Grade 3-4 (%) | Grades 1-4 (%) | Grade 3-4 (%)
Anemia^1,2 | 98 | 28 | 91 | 7
Neutropenia^1,3 | 85 | 47 | 83 | 58
Thrombocytopenia^1,3 | 68 | 18 | 55 | 9
^1 508 patients assessed in protein bound paclitaxel/carboplatin-treated group.
^2 514 patients assessed in paclitaxel injection/carboplatin-treated group.
^3 513 patients assessed in paclitaxel injection/carboplatin-treated group.

Table 8 provides the frequency and severity of adverse reactions, which occurred with a difference of ≥ 5% for all grades (1-4) or ≥ 2% for Grade 3-4 between either treatment group for the 514 protein bound paclitaxel plus carboplatin-treated patients compared with the 524 patients who received paclitaxel injection plus carboplatin.

Table 8: Selected Adverse Reactions with a Difference of ≥5% for All Grade Toxicity or ≥2% for Grade 3-4 Toxicity Between Treatment Groups
System Organ; Class | Adverse Reaction | Protein Bound Paclitaxel (100 mg/m^2 weekly) + carboplatin; (N=514) |  | Paclitaxel Injection (200 mg/m^2; every 3 weeks) + carboplatin; (N=524)
System Organ; Class | Adverse Reaction | Grades 1-4; Toxicity; (%) | Grade 3-4; Toxicity; (%) | Grades 1-4; Toxicity; (%) | Grade 3-4; Toxicity; (%)
Nervous system disorders | Peripheral neuropathya | 48 | 3 | 64 | 12
General disorders and administration site conditions | Edema peripheral | 10 | 0 | 4 | <1
Respiratory thoracic and mediastinal disorders | Epistaxis | 7 | 0 | 2 | 0
Musculoskeletal and connective tissue disorders | Arthralgia | 13 | <1 | 25 | 2
Musculoskeletal and connective tissue disorders | Myalgia | 10 | <1 | 19 | 2
a Peripheral neuropathy is defined by the MedDRA Version 14.0 SMQ neuropathy (broad scope).

For the protein bound paclitaxel plus carboplatin treated group, 17/514 (3%) patients developed Grade 3 peripheral neuropathy and no patients developed Grade 4 peripheral neuropathy. Grade 3 neuropathy improved to Grade 1 or resolved in 10/17 patients (59%) following interruption or discontinuation of protein bound paclitaxel.

Adenocarcinoma of the Pancreas

Adverse reactions were assessed in 421 patients who received protein bound paclitaxel plus gemcitabine and 402 patients who received gemcitabine for the first-line systemic treatment of metastatic adenocarcinoma of the pancreas in a multicenter, multinational, randomized, controlled, open-label trial. Patients received a median treatment duration of 3.9 months in the protein bound paclitaxel/gemcitabine group and 2.8 months in the gemcitabine group. For the treated population, the median relative dose intensity for gemcitabine was 75% in the protein bound paclitaxel/gemcitabine group and 85% in the gemcitabine group. The median relative dose intensity of protein bound paclitaxel was 81%.

Table 9 provides the frequency and severity of laboratory-detected abnormalities which occurred at a higher incidence for Grades 1-4 (≥5%) or for Grade 3-4 (≥2%) toxicity in protein bound paclitaxel plus gemcitabine-treated patients.

Table 9: Selected Hematologic Laboratory-Detected Abnormalities with a Higher Incidence (≥5% for Grades 1-4 or ≥2% for Grades 3-4 Events) in the Protein Bound Paclitaxel/Gemcitabine Arm
 | Protein Bound Paclitaxel (125 mg/m^2)/
 | Gemcitabined |  | Gemcitabine
 | Grades 1-4 | Grade 3-4 | Grades 1-4 | Grade 3-4
 | (%) | (%) | (%) | (%)
Neutropeniaa,b | 73 | 38 | 58 | 27
Thrombocytopeniab,c | 74 | 13 | 70 | 9
a 405 patients assessed in protein bound paclitaxel/gemcitabine-treated group.
b 388 patients assessed in gemcitabine-treated group.
c 404 patients assessed in protein bound paclitaxel/gemcitabine-treated group.
d Neutrophil growth factors were administered to 26% of patients in the protein bound paclitaxel/gemcitabine group.

Table 10 provides the frequency and severity of adverse reactions which occurred with a difference of ≥ 5% for all grades or ≥ 2% for Grade 3 or higher in the protein bound paclitaxel plus gemcitabine-treated group compared to the gemcitabine group.

Table 10: Selected Adverse Reactions with a Higher Incidence (≥5% for All Grade Toxicity or ≥2% for Grade 3 or Higher Toxicity) in the Protein Bound Paclitaxel/Gemcitabine Arm
System Organ Class | Adverse Reaction | Protein Bound Paclitaxel (125 mg/m^2) and gemcitabine; (N=421) |  | Gemcitabine; (N=402)
System Organ Class | Adverse Reaction | All Grades | Grade 3 or Higher | All Grades | Grade 3 or Higher
General disorders and administration site conditions | Fatigue | 248 (59%) | 77 (18%) | 183 (46%) | 37 (9%)
General disorders and administration site conditions | Peripheral edema | 194 (46%) | 13 (3%) | 122 (30%) | 12 (3%)
General disorders and administration site conditions | Pyrexia | 171 (41%) | 12 (3%) | 114 (28%) | 4 (1%)
General disorders and administration site conditions | Asthenia | 79 (19%) | 29 (7%) | 54 (13%) | 17 (4%)
General disorders and administration site conditions | Mucositis | 42 (10%) | 6 (1%) | 16 (4%) | 1 (<1%)
Gastrointestinal disorders | Nausea | 228 (54%) | 27 (6%) | 192 (48%) | 14 (3%)
Gastrointestinal disorders | Diarrhea | 184 (44%) | 26 (6%) | 95 (24%) | 6 (1%)
Gastrointestinal disorders | Vomiting | 151 (36%) | 25 (6%) | 113 (28%) | 15 (4%)
Skin and subcutaneous tissue disorders | Alopecia | 212 (50%) | 6 (1%) | 21 (5%) | 0
Skin and subcutaneous tissue disorders | Rash | 128 (30%) | 8 (2%) | 45 (11%) | 2 (<1%)
Nervous system disorders | Peripheral neuropathya | 227 (54%) | 70 (17%) | 51 (13%) | 3 (1%)
Nervous system disorders | Dysgeusia | 68 (16%) | 0 | 33 (8%) | 0
Nervous system disorders | Headache | 60 (14%) | 1 (<1%) | 38 (9%) | 1 (<1%)
Metabolism and nutrition disorders | Decreased appetite | 152 (36%) | 23 (5%) | 104 (26%) | 8 (2%)
Metabolism and nutrition disorders | Dehydration | 87 (21%) | 31 (7%) | 45 (11%) | 10 (2%)
Metabolism and nutrition disorders | Hypokalemia | 52 (12%) | 18 (4%) | 28 (7%) | 6 (1%)
Respiratory, thoracic and mediastinal disorders | Cough | 72 (17%) | 0 | 30 (7%) | 0
Respiratory, thoracic and mediastinal disorders | Epistaxis | 64 (15%) | 1 (<1%) | 14 (3%) | 1 (<1%)
Infections and infestations | Urinary tract infectionsb | 47 (11%) | 10 (2%) | 20 (5%) | 1 (<1%)
Musculoskeletal and connective | Pain in extremity | 48 (11%) | 3 (1%) | 24 (6%) | 3 (1%)
tissue disorders | Arthralgia | 47 (11%) | 3 (1%) | 13 (3%) | 1 (<1%)
 | Myalgia | 44 (10%) | 4 (1%) | 15 (4%) | 0
Psychiatric disorders | Depression | 51 (12%) | 1 (<1%) | 24 (6%) | 0
a Peripheral neuropathy is defined by the MedDRA Version 15.0 Standard MedDRA Query neuropathy (broad scope).
b Urinary tract infections includes the preferred terms of: urinary tract infection, cystitis, urosepsis, urinary tract infection bacterial, and urinary tract infection enterococcal.

Additional clinically relevant adverse reactions that were reported in <10% of the patients with adenocarcinoma of the pancreas who received protein bound paclitaxel/gemcitabine included:

Infections and Infestations: oral candidiasis, pneumonia

Vascular Disorders: hypertension

Cardiac Disorders: tachycardia, congestive cardiac failure

Eye Disorders: cystoid macular edema

Peripheral Neuropathy

Grade 3 peripheral neuropathy occurred in 17% of patients who received protein bound paclitaxel/gemcitabine compared to 1% of patients who received gemcitabine only; no patients developed Grade 4 peripheral neuropathy. The median time to first occurrence of Grade 3 peripheral neuropathy in the protein bound paclitaxel arm was 140 days. Upon suspension of protein bound paclitaxel dosing, the median time to improvement from Grade 3 peripheral neuropathy to ≤ Grade 1 was 29 days. Of protein bound paclitaxel-treated patients with Grade 3 peripheral neuropathy, 44% resumed protein bound paclitaxel at a reduced dose.

Sepsis

Sepsis occurred in 5% of patients who received protein bound paclitaxel/gemcitabine compared to 2% of patients who received gemcitabine alone. Sepsis occurred both in patients with and without neutropenia. Risk factors for sepsis included biliary obstruction or presence of biliary stent.

Pneumonitis

Pneumonitis occurred in 4% of patients who received protein bound paclitaxel/gemcitabine compared to 1% of patients who received gemcitabine alone. Two of 17 patients in the protein bound paclitaxel arm with pneumonitis died.

6.2 Postmarketing Experience

The following adverse reactions have been identified during postapproval use of protein bound paclitaxel or with paclitaxel injection and may be expected to occur with Paclitaxel Protein-Bound Particles for Injectable Suspension (albumin-bound). Because these reactions are reported voluntarily from a population of uncertain size, it is not always possible to reliably estimate their frequency or establish a causal relationship to drug exposure.

Hypersensitivity Reactions

Severe and sometimes fatal hypersensitivity reactions. Cross-hypersensitivity between protein bound paclitaxel and other taxanes has been reported.

Cardiovascular

Congestive heart failure, left ventricular dysfunction, and atrioventricular block. Most patients were previously exposed to cardiotoxic drugs, such as anthracyclines, or had underlying cardiac history.

Respiratory

Pneumonitis, interstitial pneumonia, and pulmonary embolism

Radiation pneumonitis in patients receiving concurrent radiotherapy.

Lung fibrosis has been reported with paclitaxel injection.

Neurologic

Cranial nerve palsies and vocal cord paresis, as well as autonomic neuropathy resulting in paralytic ileus.

Vision Disorders

Reduced visual acuity due to cystoid macular edema (CME). After cessation of treatment, CME may improve, and visual acuity may return to baseline. Abnormal visual evoked potentials in patients treated with paclitaxel injection suggest persistent optic nerve damage.

Hepatic

Hepatic necrosis and hepatic encephalopathy leading to death in patients treated with paclitaxel injection.

Gastrointestinal (GI)

Intestinal obstruction, intestinal perforation, pancreatitis, and ischemic colitis. In patients treated with paclitaxel injection, neutropenic enterocolitis (typhlitis) despite the coadministration of G-CSF, alone and in combination with other chemotherapeutic agents.

Injection Site Reaction

Extravasation. Closely monitor the Paclitaxel Protein-Bound Particles for Injectable Suspension (albumin-bound) infusion site for possible infiltration during drug administration [see Dosage and Administration 2.1)].

Severe events such as phlebitis, cellulitis, induration, necrosis, and fibrosis have been reported with paclitaxel injection. In some cases, the onset of the injection site reaction occurred during a prolonged infusion or was delayed up to ten days. Recurrence of skin reactions at a site of previous extravasation following administration of paclitaxel injection at a different site has been reported.

Metabolic and Nutritional Disorders

Tumor lysis syndrome

Other Clinical Events

Skin reactions including generalized or maculopapular rash, erythema, and pruritus.

Photosensitivity reactions, radiation recall phenomenon, scleroderma, and in some patients previously exposed to capecitabine, reports of palmar-plantar erythrodysesthesia. Stevens-Johnson syndrome and toxic epidermal necrolysis have been reported.

Conjunctivitis, cellulitis, and increased lacrimation have been reported with paclitaxel injection.

Accidental Exposure

Upon inhalation of paclitaxel, dyspnea, chest pain, burning eyes, sore throat, and nausea have been reported.

Following topical exposure, tingling, burning, and redness have been reported.

7 DRUG INTERACTIONS

7.1 Effect of Other Drugs on Paclitaxel Protein-Bound Particles for Injectable Suspension

The metabolism of paclitaxel is catalyzed by CYP2C8 and CYP3A4. Caution should be exercised when administering protein bound paclitaxel concomitantly with medicines known to inhibit or induce either CYP2C8 or CYP3A4 [see Clinical Pharmacology (12.3)].

8 USE IN SPECIFIC POPULATIONS

8.1 Pregnancy

Risk Summary

Based on its mechanism of action and findings in animals, Paclitaxel Protein-Bound Particles for Injectable Suspension (albumin-bound) can cause fetal harm when administered to a pregnant woman [see Clinical Pharmacology (12.1)]. There are no available human data on Paclitaxel Protein-Bound Particles for Injectable Suspension (albumin-bound) use in pregnant women to inform the drug-associated risk.

In animal reproduction studies, administration of paclitaxel formulated as albumin-bound particles to pregnant rats during the period of organogenesis resulted in embryo-fetal toxicity at doses approximately 2% of the daily maximum recommended human dose on a mg/m^2 basis (see Data). Advise females of reproductive potential of the potential risk to a fetus.

The background rate of major birth defects and miscarriage is unknown for the indicated population. In the U.S. general population, the estimated background risk of major birth defects and miscarriage in clinically recognized pregnancies is 2% to 4% and 15% to 20%, respectively.

Data

Animal Data

In embryo-fetal development studies, intravenous administration of paclitaxel formulated as albumin-bound particles to rats during pregnancy, on gestation days 7 to 17 at doses of 6 mg/m^2 (approximately 2% of the daily maximum recommended human dose on a mg/m^2 basis) caused embryo-fetal toxicities, as indicated by intrauterine mortality, increased resorptions (up to 5-fold), reduced numbers of litters and live fetuses, reduction in fetal body weight, and increase in fetal anomalies. Fetal anomalies included soft tissue and skeletal malformations, such as eye bulge, folded retina, microphthalmia, and dilation of brain ventricles.

8.2 Lactation

Risk Summary

There are no data on the presence of paclitaxel in human milk, or its effect on the breastfed child or on milk production. In animal studies, paclitaxel and/or its metabolites were excreted into the milk of lactating rats (see Data). Because of the potential for serious adverse reactions in a breastfed child, advise lactating women not to breastfeed during treatment with Paclitaxel Protein-Bound Particles for Injectable Suspension (albumin-bound) and for two weeks after the last dose.

Data

Animal Data

Following intravenous administration of radiolabeled paclitaxel to rats on days 9 to 10 postpartum, concentrations of radioactivity in milk were higher than in plasma and declined in parallel with the plasma concentrations.

8.3 Females and Males of Reproductive Potential

Based on animal studies and mechanism of action, Paclitaxel Protein-Bound Particles for Injectable Suspension (albumin-bound) can cause fetal harm when administered to a pregnant woman [see Use in Specific Populations (8.1)].

Pregnancy Testing

Verify the pregnancy status of females of reproductive potential prior to starting treatment with Paclitaxel Protein-Bound Particles for Injectable Suspension (albumin-bound).

Contraception

Females

Advise females of reproductive potential to use effective contraception and avoid becoming pregnant during treatment with Paclitaxel Protein-Bound Particles for Injectable Suspension (albumin-bound) and for at least six months after the last dose.

Males

Based on findings in genetic toxicity and animal reproduction studies, advise males with female partners of reproductive potential to use effective contraception and avoid fathering a child during treatment with Paclitaxel Protein-Bound Particles for Injectable Suspension (albumin-bound) and for at least three months after the last dose [see Use in Specific Populations (8.1) and Nonclinical Toxicology (13.1)].

Infertility

Females and Males

Based on findings in animals, Paclitaxel Protein-Bound Particles for Injectable Suspension (albumin-bound) may impair fertility in females and males of reproductive potential [see Nonclinical Toxicology (13.1)].

8.4 Pediatric Use

Safety and effectiveness in pediatric patients have not been established. Pharmacokinetics, safety, and antitumor activity of Paclitaxel Protein-Bound Particles for Injectable Suspension (albumin-bound) were assessed in an open-label, dose escalation, dose expansion study (NCT01962103) in 96 pediatric patients aged 1.4 to < 17 years with recurrent or refractory pediatric solid tumors. The maximum tolerated dose (MTD) normalized for body surface area (BSA) was lower in pediatric patients compared to adults. No new safety signals were observed in pediatric patients across these studies.

Paclitaxel protein-bound exposures normalized by dose were higher in 96 pediatric patients (aged 1.4 to < 17 years) as compared to those in adults.

8.5 Geriatric Use

Of the 229 patients in the randomized study who received protein bound paclitaxel for the treatment of metastatic breast cancer, 13% were at least 65 years of age and <2% were 75 years or older. This study of protein bound paclitaxel did not include a sufficient number of patients with metastatic breast cancer who were 65 years and older to determine whether they respond differently from younger patients.

A subsequent pooled analysis was conducted in 981 patients receiving protein bound paclitaxel monotherapy for metastatic breast cancer, of which 15% were 65 years of age or older and 2% were 75 years of age or older. A higher incidence of epistaxis, diarrhea, dehydration, fatigue, and peripheral edema was found in patients
65 years of age or older.

Of the 514 patients in the randomized study who received protein bound paclitaxel and carboplatin for the first-line treatment of non-small cell lung cancer, 31% were 65 years or older and 3.5% were 75 years or older. Myelosuppression, peripheral neuropathy, and arthralgia were more frequent in patients 65 years or older compared to patients younger than 65 years old. No overall difference in effectiveness, as measured by response rates, was observed between patients 65 years or older compared to patients younger than 65 years old.

Of the 431 patients in the randomized study who received protein bound paclitaxel and gemcitabine for the first-line treatment of pancreatic adenocarcinoma, 41% were 65 years or older and 10% were 75 years or older. No overall differences in effectiveness were observed between patients who were 65 years of age or older and younger patients. Diarrhea, decreased appetite, dehydration, and epistaxis were more frequent in patients 65 years or older compared with patients younger than 65 years old. Clinical studies of protein bound paclitaxel did not include sufficient number of patients with pancreatic cancer who were 75 years and older to determine whether they respond differently from younger patients.

8.6 Renal Impairment

No adjustment of the starting Paclitaxel Protein-Bound Particles for Injectable Suspension (albumin-bound) dose is required for patients with mild to moderate renal impairment (estimated creatinine clearance 30 to <90 mL/min) [see Clinical Pharmacology (12.3)]. There are insufficient data to permit dosage recommendations in patients with severe renal impairment or end stage renal disease (estimated creatinine clearance <30 mL/min).

8.7 Hepatic Impairment

Paclitaxel Protein-Bound Particles for Injectable Suspension (albumin-bound) is not recommended for use in patients with total bilirubin > 5 x ULN or AST > 10 x ULN [see Dosage and Administration (2.3), Warnings and Precautions (5.6), and Clinical Pharmacology (12.3)].

Reduce Paclitaxel Protein-Bound Particles for Injectable Suspension (albumin-bound) starting dose in patients with moderate to severe hepatic impairment (total bilirubin > 1.5 x ULN and ≤ 5 x ULN and AST ≤ 10 x ULN) [see Dosage and Administration (2.5) and Clinical Pharmacology (12.3)].

No adjustment of the starting Paclitaxel Protein-Bound Particles for Injectable Suspension (albumin-bound) dose is required for patients with mild hepatic impairment (total bilirubin > ULN and ≤ 1.5 x ULN and aspartate aminotransferase [AST] ≤ 10 x ULN).

10 OVERDOSAGE

There is no known antidote for Paclitaxel Protein-Bound Particles for Injectable Suspension (albumin-bound) overdosage. The primary anticipated complications of overdosage would consist of bone marrow suppression, sensory neurotoxicity, and mucositis.

11 DESCRIPTION

Paclitaxel Protein-Bound Particles for Injectable Suspension (albumin-bound) is paclitaxel, formulated as albumin-bound nanoparticles with a mean particle size of approximately 130 nanometers. Paclitaxel exists in the particles in a non-crystalline, amorphous state. Paclitaxel is a microtubule inhibitor. The chemical name for paclitaxel is 5β,20-Epoxy-1,2α,4,7β,10β,13α-hexahydroxytax-11-en-9-one 4,10-diacetate 2-benzoate 13-ester with (2R,3S)-N-benzoyl-3-phenylisoserine. The molecular formula is C47H51NO14 and the molecular weight is 853.91. Paclitaxel has the following structural formula:

Paclitaxel is a white to off-white crystalline powder. It is highly lipophilic, insoluble in water, and melts at approximately 216°C to 217°C.

Paclitaxel Protein-Bound Particles for Injectable Suspension (albumin-bound) is supplied as a white to yellow, sterile, lyophilized powder for reconstitution with 20 mL of 0.9% Sodium Chloride Injection prior to intravenous infusion. Each single-dose vial contains 100 mg of paclitaxel, approximately 900 mg of human albumin (containing sodium caprylate and sodium acetyltryptophanate), and approximately 23 mg sodium chloride. Each milliliter (mL) of reconstituted suspension contains 5 mg paclitaxel. Paclitaxel Protein-Bound Particles for Injectable Suspension (albumin-bound) is free of solvents.

12 CLINICAL PHARMACOLOGY

12.1 Mechanism of Action

Paclitaxel Protein-Bound Particles for Injectable Suspension (albumin-bound) is a microtubule inhibitor that promotes the assembly of microtubules from tubulin dimers and stabilizes microtubules by preventing depolymerization. This stability results in the inhibition of the normal dynamic reorganization of the microtubule network that is essential for vital interphase and mitotic cellular functions. Paclitaxel induces abnormal arrays or “bundles” of microtubules throughout the cell cycle and multiple asters of microtubules during mitosis.

12.3 Pharmacokinetics

The pharmacokinetics of total paclitaxel following 30- and 180-minute infusions of protein bound paclitaxel at dose levels of 80 to 375 mg/m^2 (0.31 to 1.15 times the maximum approved recommended dosage) were determined in clinical studies. Dose levels of mg/m^2 refer to mg of paclitaxel in protein bound paclitaxel. Following intravenous administration of protein bound paclitaxel to patients with solid tumors, paclitaxel plasma concentrations declined in a biphasic manner, the initial rapid decline representing distribution to the peripheral compartment and the slower second phase representing drug elimination.

Following protein bound paclitaxel infusion, paclitaxel exhibited linear drug exposure (AUC) across clinical doses ranging from 80 to 300 mg/m^2 (0.31 to 1.15 times the maximum approved recommended dosage). The pharmacokinetics of paclitaxel in protein bound paclitaxel were independent of the duration of intravenous administration.

The pharmacokinetic data of 260 mg/m^2 protein bound paclitaxel administered over a 30-minute infusion was compared to the pharmacokinetics of 175 mg/m^2 paclitaxel injection over a 3-hour infusion. Clearance was larger (43%) and the volume of distribution was higher (53%) for protein bound paclitaxel than for paclitaxel injection. There were no differences in terminal half-lives.

Distribution

Following protein bound paclitaxel administration to patients with solid tumors, paclitaxel is evenly distributed into blood cells and plasma and is highly bound to plasma proteins (94%). The total volume of distribution is approximately 1,741 L; the large volume of distribution indicates extensive extravascular distribution and/or tissue binding of paclitaxel.

In a within-patient comparison study, the fraction of unbound paclitaxel in plasma was significantly higher with protein bound paclitaxel (6.2%) than with solvent-based paclitaxel (2.3%). This contributes to significantly higher exposure to unbound paclitaxel with protein bound paclitaxel compared with solvent-based paclitaxel, when the total exposure is comparable. In vitro studies of binding to human serum proteins, using paclitaxel concentrations ranging from 0.1 to 50 mcg/mL, indicated that the presence of cimetidine, ranitidine, dexamethasone, or diphenhydramine did not affect protein binding of paclitaxel.

Elimination

At the clinical dose range of 80 to 300 mg/m^2 (0.31 to 1.15 times the maximum approved recommended dosage), the mean total clearance of paclitaxel ranges from 13 to 30 L/h/m^2 and the mean terminal half-life ranges from 13 to 27 hours.

Metabolism

In vitro studies with human liver microsomes and tissue slices showed that paclitaxel in protein bound paclitaxel was metabolized primarily to 6α-hydroxypaclitaxel by CYP2C8; and to two minor metabolites, 3’-p-hydroxypaclitaxel and 6α, 3’-p-dihydroxypaclitaxel, by CYP3A4. In vitro, the metabolism of paclitaxel to 6α-hydroxypaclitaxel was inhibited by a number of agents (ketoconazole, verapamil, diazepam, quinidine, dexamethasone, cyclosporin, teniposide, etoposide, and vincristine), but the concentrations used exceeded those found in vivo following normal therapeutic doses. Testosterone, 17α-ethinyl estradiol, retinoic acid, and quercetin, a specific inhibitor of CYP2C8, also inhibited the formation of 6α-hydroxypaclitaxel in vitro. The pharmacokinetics of paclitaxel may also be altered in vivo as a result of interactions with compounds that are substrates, inducers, or inhibitors of CYP2C8 and/or CYP3A4 [see Drug Interactions (7)].

Excretion

After a 30-minute infusion of 260 mg/m^2 doses of protein bound paclitaxel, the mean values for cumulative urinary recovery of unchanged drug (4%) indicated extensive non-renal clearance. Less than 1% of the total administered dose was excreted in urine as the metabolites 6α-hydroxypaclitaxel and 3’-p-hydroxypaclitaxel. Fecal excretion was approximately 20% of the total dose administered.

Specific Populations

No clinically meaningful differences in the pharmacokinetics of paclitaxel in protein bound paclitaxel were observed based on body weight (40 to 143 kg), body surface area (1.3 to 2.4 m^2), sex, race (Asian vs. White), age (24 to 85 years), type of solid tumors, mild to moderate renal impairment (creatinine clearance 30 to <90 mL/min), and mild hepatic impairment (total bilirubin >1 to ≤1.5 x ULN and AST ≤10 x ULN).

Patients with moderate (total bilirubin >1.5 to 3 x ULN and AST ≤10 x ULN) or severe (total bilirubin >3 to 5 x ULN) hepatic impairment had a 22% to 26% decrease in the maximum elimination rate of paclitaxel and approximately 20% increase in mean paclitaxel AUC compared with patients with normal hepatic function (total bilirubin ≤ULN and AST ≤ULN) [see Dosage and Administration (2.5) and Use in Specific Populations (8.7)].

The effect of severe renal impairment or end stage renal disease (creatinine clearance <30 mL/min) on the pharmacokinetics of paclitaxel in protein bound paclitaxel is unknown.

Drug Interaction Studies

Carboplatin: Administration of carboplatin immediately after the completion of the protein bound paclitaxel infusion to patients with NSCLC did not cause clinically meaningful changes in paclitaxel exposure. The observed mean AUCinf of free carboplatin was approximately 23% higher than the targeted value
(6 min*mg/mL), but its mean half-life and clearance were consistent with those reported in the absence of paclitaxel.

13 NONCLINICAL TOXICOLOGY

13.1 Carcinogenesis, Mutagenesis, Impairment of Fertility

The carcinogenic potential of Paclitaxel Protein-Bound Particles for Injectable Suspension (albumin-bound) has not been studied.

Paclitaxel was clastogenic in vitro (chromosome aberrations in human lymphocytes) and in vivo (micronucleus test in mice). Paclitaxel was not mutagenic in the Ames test or the CHO/HGPRT gene mutation assay.

Administration of paclitaxel formulated as albumin-bound particles to male rats at 42 mg/m^2 on a weekly basis (approximately 16% of the daily maximum recommended human exposure on a body surface area basis) for 11 weeks prior to mating with untreated female rats resulted in significantly reduced fertility accompanied by decreased pregnancy rates and increased loss of embryos in mated females. A dose of 42 mg/m^2 also reduced male reproductive organ weights, mating performance, and sperm production. Testicular atrophy/degeneration was observed in single-dose toxicology studies in animals administered paclitaxel formulated as albumin-bound particles at doses lower than the recommended human dose; doses were 54 mg/m^2 in rodents and 175 mg/m^2 in dogs. Similar testicular degeneration was seen in monkeys administered three weekly doses of 108 mg/m^2 paclitaxel formulated as albumin bound particles.

Administration of paclitaxel prior to and during mating produced impairment of fertility in male and female rats. Paclitaxel caused reduced fertility and reproductive indices, and increased embryo-fetal toxicity.

14 CLINICAL STUDIES

14.1 Metastatic Breast Cancer

Data from 106 patients accrued in two single arm open label studies and from 460 patients enrolled in a randomized comparative study were available to support the use of protein bound paclitaxel in metastatic breast cancer.

Single Arm Open Label Studies

In one study, protein bound paclitaxel was administered as a 30-minute infusion at a dose of 175 mg/m^2 to 43 patients with metastatic breast cancer. The second trial utilized a dose of 300 mg/m^2 as a 30-minute infusion in 63 patients with metastatic breast cancer. Cycles were administered at 3-week intervals. Objective responses were observed in both studies.

Randomized Comparative Study

This multicenter trial was conducted in 460 patients with metastatic breast cancer. Patients were randomized to receive protein bound paclitaxel at a dose of 260 mg/m^2 given as a 30-minute infusion, or paclitaxel injection at 175 mg/m^2 given as a 3-hour infusion. Sixty-four percent of patients had impaired performance status (ECOG 1 or 2) at study entry; 79% had visceral metastases; and 76% had >3 sites of metastases. Fourteen percent of the patients had not received prior chemotherapy; 27% had received chemotherapy in the adjuvant setting, 40% in the metastatic setting and 19% in both metastatic and adjuvant settings. Fifty-nine percent received study drug as second or greater than second-line therapy. Seventy-seven percent of the patients had been previously exposed to anthracyclines.

In this trial, patients in the protein bound paclitaxel treatment arm had a statistically significantly higher reconciled target lesion response rate (the trial primary endpoint) of 21.5% (95% CI: 16.2% to 26.7%), compared to 11.1% (95% CI: 6.9% to 15.1%) for patients in the paclitaxel injection treatment arm. See Table 11. There was no statistically significant difference in overall survival between the two study arms.

Table 11: Efficacy Results from Randomized Metastatic Breast Cancer Trial
 |  | Protein Bound Paclitaxel 260 mg/m^2 |  | Paclitaxel Injection; 175 mg/m^2
Reconciled Target Lesion Response Rate (primary endpoint)a
All randomized patients | Response Rate; [95% CI] |  | 50/233 (21.5%); [16.19% to 26.73%] | 25/227 (11.1%); [6.94% to 15.09%]
All randomized patients | p-valueb |  | 0.003
Patients who had failed combination chemotherapy or relapsed within 6 months of adjuvant chemotherapyc | Response Rate; [95% CI] |  | 20/129 (15.5%); [9.26% to 21.75%] | 12/143 (8.4%); [3.85% to 12.94%]
a Reconciled Target Lesion Response Rate (TLRR) was the prospectively defined protocol specific endpoint, based on independent radiologic assessment of tumor responses reconciled with investigator responses (which also included clinical information) for the first 6 cycles of therapy. The reconciled TLRR was lower than the investigator Reported Response Rates, which are based on all cycles of therapy.
b From Cochran-Mantel-Haenszel test stratified by 1st line vs. >1st line therapy.
c Prior therapy included an anthracycline unless clinically contraindicated.

14.2 Non-Small Cell Lung Cancer

A multicenter, randomized, open-label study was conducted in 1,052 chemotherapy naive patients with Stage IIIb/IV non-small cell lung cancer to compare protein bound paclitaxel in combination with carboplatin to paclitaxel injection in combination with carboplatin as first-line treatment in patients with advanced non-small cell lung cancer. protein bound paclitaxel was administered as an intravenous infusion over 30 minutes at a dose of 100 mg/m^2 on Days 1, 8, and 15 of each 21-day cycle. Paclitaxel injection was administered as an intravenous infusion over 3 hours at a dose of 200 mg/m^2, following premedication. In both treatment arms carboplatin at a dose of AUC = 6 mg•min/mL was administered intravenously on Day 1 of each 21-day cycle after completion of protein bound paclitaxel/paclitaxel infusion. Treatment was administered until disease progression or development of an unacceptable toxicity. The major efficacy outcome measure was overall response rate as determined by a central independent review committee using RECIST guidelines (Version 1.0).

In the intent-to-treat (all-randomized) population, the median age was 60 years, 75% were men, 81% were White, 49% had adenocarcinoma, 43% had squamous cell lung cancer, 76% were ECOG PS 1, and 73% were current or former smokers. Patients received a median of 6 cycles of treatment in both study arms.

Patients in the protein bound paclitaxel /carboplatin arm had a statistically significantly higher overall response rate compared to patients in the paclitaxel injection/carboplatin arm [(33% versus 25%) see Table 12]. There was no statistically significant difference in overall survival between the two study arms.

Table 12: Efficacy Results from Randomized Non-Small Cell Lung Cancer Trial (Intent-to-Treat Population)
 | Protein Bound Paclitaxel (100 mg/m^2 weekly) + carboplatin; (N=521) | Paclitaxel Injection; (200 mg/m^2 every 3 weeks) + carboplatin; (N=531)
Overall Response Rate (ORR)
Confirmed complete or partial overall response, n (%) | 170 (33%) | 132 (25%)
95% CI | 28.6, 36.7 | 21.2, 28.5
P-value (Chi-Square test) | 0.005
Median DoR in months (95% CI) | 6.9 (5.6, 8.0) | 6.0 (5.6, 7.1)
Overall Response Rate by Histology
Carcinoma/Adenocarcinoma | 66/254 (26%) | 71/264 (27%)
Squamous Cell Carcinoma | 94/229 (41%) | 54/221 (24%)
Large Cell Carcinoma | 3/9 (33%) | 2/13 (15%)
Other | 7/29 (24%) | 5/33 (15%)
CI = confidence interval; DoR= Duration of response.

14.3 Adenocarcinoma of the Pancreas

A multicenter, multinational, randomized, open-label study was conducted in 861 patients comparing protein bound paclitaxel plus gemcitabine versus gemcitabine monotherapy as first-line treatment of metastatic adenocarcinoma of the pancreas. Key eligibility criteria were Karnofsky Performance Status (KPS) ≥70, normal bilirubin level, transaminase levels ≤ 2.5 times the upper limit of normal (ULN) or ≤ 5 times the ULN for patients with liver metastasis, no prior cytotoxic chemotherapy in the adjuvant setting or for metastatic disease, no ongoing active infection requiring systemic therapy, and no history of interstitial lung disease. Patients with rapid decline in KPS (≥10%) or serum albumin (≥20%) during the 14 day screening period prior to study randomization were ineligible.

A total of 861 patients were randomized (1:1) to the protein bound paclitaxel/gemcitabine arm (N=431) or to the gemcitabine arm (N=430).

Randomization was stratified by geographic region (Australia, Western Europe, Eastern Europe, or North America), KPS (70 to 80 versus 90 to 100), and presence of liver metastasis (yes versus no). Patients randomized to protein bound paclitaxel/gemcitabine received protein bound paclitaxel 125 mg/m^2 as an intravenous infusion over 30 to 40 minutes followed by gemcitabine 1000 mg/m^2 as an intravenous infusion over 30 to 40 minutes on Days 1, 8, and 15 of each 28-day cycle. Patients randomized to gemcitabine received 1,000 mg/m^2 as an intravenous infusion over 30 to 40 minutes weekly for 7 weeks followed by a 1-week rest period in Cycle 1 then as 1,000 mg/m^2 on Days 1, 8, and 15 of each subsequent 28-day cycle. Patients in both arms received treatment until disease progression or unacceptable toxicity. The major efficacy outcome measure was overall survival (OS). Additional outcome measures were progression-free survival (PFS) and overall response rate (ORR), both assessed by independent, central, blinded radiological review using RECIST (version 1.0).

In the intent-to-treat (all randomized) population, the median age was 63 years (range 27 to 88 years) with
42% ≥ 65 years of age; 58% were men; 93% were White and KPS was 90 to 100 in 60%. Disease characteristics included 46% of patients with 3 or more metastatic sites; 84% of patients had liver metastasis; and the location of the primary pancreatic lesion was in the head of pancreas (43%), body (31%), or tail (25%).

Results for overall survival, progression-free survival, and overall response rate are shown in Table 13.

Table 13: Efficacy Results from Randomized Study in Patients with Adenocarcinoma of the Pancreas (ITT Population)
 | Protein Bound Paclitaxel (125 mg/m^2) and gemcitabine; (N = 431) | Gemcitabine; (N = 430)
Overall Survival
Number of deaths, n (%) | 333 (77) | 359 (83)
Median Overall Survival (months) | 8.5 | 6.7
95% CI | 7.9, 9.5 | 6.0, 7.2
HR (95% CI)a | 0.72 (0.62, 0.83)
P-valueb | <0.0001
Progression-free Survivalc
Death or progression, n (%) | 277 (64) | 265 (62)
Median Progression-free Survival (months) | 5.5 | 3.7
95% CI | 4.5, 5.9 | 3.6, 4.0
HR (95% CI)a | 0.69 (0.58, 0.82)
P-valueb | <0.0001
Overall Response Ratec
Confirmed complete or partial overall response, n (%) | 99 (23) | 31 (7)
95% CI | 19.1, 27.2 | 5.0, 10.1
P-valued | <0.0001
CI = confidence interval, HR = hazard ratio of protein bound paclitaxel plus gemcitabine / gemcitabine, ITT = intent-to-treat population.
a Stratified Cox proportional hazard model.
b Stratified log-rank test stratified by geographic region (North America versus Others), Karnofsky performance score (70 to 80 versus 90 to 100), and presence of liver metastasis (yes versus no).
c Based on Independent Radiological Reviewer Assessment.
d Chi-square test.

In exploratory analyses conducted in clinically relevant subgroups with a sufficient number of subjects, the treatment effects on overall survival were similar to that observed in the overall study population.

Figure 1: Kaplan-Meier Curve of Overall Survival (Intent-to-Treat Population)

15 REFERENCES

1. OSHA Hazardous Drugs. OSHA http://www.osha.gov/SLTC/hazardousdrugs/index.html

16 HOW SUPPLIED/STORAGE AND HANDLING

Paclitaxel Protein-Bound Particles for Injectable Suspension (albumin-bound) is supplied as a white to yellow, sterile, lyophilized powder for reconstitution and is available as follows:

NDC 0480-3290-01 100 mg of paclitaxel in a single-dose vial, individually packaged in a carton.

Store vial in original carton at 20°C to 25°C (68°F to 77°F) [see USP Controlled Room Temperature]. Retain in the original package to protect from light.

Paclitaxel Protein-Bound Particles for Injectable Suspension (albumin-bound) is a hazardous drug. Follow applicable special handling and disposal procedures.^1

17 PATIENT COUNSELING INFORMATION

Advise the patient to read the approved patient labeling (Patient Information).

Severe Myelosuppression

- Patients must be informed of the risk of low blood cell counts and severe and life-threatening infections and instructed to contact their healthcare provider immediately for fever or evidence of infection [see Warnings and Precautions (5.1), (5.3)].

Severe Neuropathy

- Patients must be informed that sensory neuropathy occurs frequently with Paclitaxel Protein-Bound Particles for Injectable Suspension (albumin-bound) and patients should advise their healthcare providers of numbness, tingling, pain, or weakness involving the extremities [see Warnings and Precautions (5.2)].

Pneumonitis

- Instruct patients to contact their healthcare provider immediately for sudden onset of dry persistent cough, or shortness of breath [see Warnings and Precautions (5.4)].

Severe Hypersensitivity

- Instruct patients to contact their healthcare provider for signs of an allergic reaction, which could be severe and sometimes fatal [see Warnings and Precautions (5.5)].

Common Adverse Reactions

- Explain to patients that alopecia, fatigue/asthenia, and myalgia/arthralgia occur frequently with Paclitaxel Protein-Bound Particles for Injectable Suspension (albumin-bound)
- Instruct patients to contact their healthcare providers for persistent vomiting, diarrhea, or signs of dehydration [see Adverse Reactions (6)].

Embryo-Fetal Toxicity

- Paclitaxel Protein-Bound Particles for Injectable Suspension (albumin-bound) can cause fetal harm. Advise patients to avoid becoming pregnant while receiving this drug. Females of reproductive potential should use effective contraception during treatment with Paclitaxel Protein-Bound Particles for Injectable Suspension (albumin-bound) and for at least six months after the last dose [see Warnings and Precautions (5.8) and Use in Specific Populations (8.1, 8.3)].
- Advise male patients with female partners of reproductive potential to use effective contraception and avoid fathering a child during treatment with Paclitaxel Protein-Bound Particles for Injectable Suspension (albumin-bound) and for at least three months after the last dose [see Use in Specific Populations (8.3)].

Lactation

- Advise patients not to breastfeed while taking Paclitaxel Protein-Bound Particles for Injectable Suspension (albumin-bound) and for two weeks after receiving the last dose [see Use in Specific Populations (8.2)].

Infertility

- Advise males and females of reproductive potential that Paclitaxel Protein-Bound Particles for Injectable Suspension (albumin-bound) may impair fertility [see Use in Specific Populations (8.3)].

Brands listed are the trademarks of their respective owners.

Manufactured By:
Pharmachemie B.V.
Haarlem, The Netherlands

Manufactured For:
Teva Pharmaceuticals
Parsippany, NJ 07054

Iss. 11/2023

PATIENT INFORMATION

PACLITAXEL (pak li tax el) protein-bound particles

for injectable suspension (albumin-bound)

What is Paclitaxel Protein-Bound Particles for Injectable Suspension (albumin-bound)?

Paclitaxel Protein-Bound Particles for Injectable Suspension (albumin-bound) is a prescription medicine used to treat:

- advanced breast cancer in people who have already received certain other medicines for their cancer.
- advanced non-small cell lung cancer (NSCLC), in combination with carboplatin in people who cannot be treated with surgery or radiation.
- advanced pancreatic cancer, when used in combination with gemcitabine as the first medicine for advanced pancreatic cancer.

It is not known if Paclitaxel Protein-Bound Particles for Injectable Suspension (albumin-bound) is safe and effective in children.

Do not receive Paclitaxel Protein-Bound Particles for Injectable Suspension (albumin-bound) if:

- your white blood cell count is below 1,500 cells/ mm^3.
- you have had a severe allergic reaction to protein bound paclitaxel.

Before you receive Paclitaxel Protein-Bound Particles for Injectable Suspension (albumin-bound), tell your healthcare provider about all of your medical conditions, including if you:

- have liver or kidney problems.
- had a prior allergic reaction to a taxane.
- are pregnant or plan to become pregnant. Paclitaxel Protein-Bound Particles for Injectable Suspension (albumin-bound) can harm your unborn baby.

Females who are able to become pregnant:

- Your healthcare provider will check to see if you are pregnant before you start treatment with Paclitaxel Protein-Bound Particles for Injectable Suspension (albumin-bound).
- You should not become pregnant during your treatment and for at least six months after your last dose of Paclitaxel Protein-Bound Particles for Injectable Suspension (albumin-bound).
- You should use effective birth control (contraception) during your treatment and for at least six months after your last dose of Paclitaxel Protein-Bound Particles for Injectable Suspension
  (albumin-bound). Talk to your healthcare provider about birth control methods you can use during this time.

Males with a female sexual partner who can become pregnant:

- Paclitaxel Protein-Bound Particles for Injectable Suspension (albumin-bound) can harm the unborn baby of your partner.
- You should not father a child during your treatment and for at least three months after your last dose of Paclitaxel Protein-Bound Particles for Injectable Suspension (albumin-bound).
- You should use effective birth control (contraception) during your treatment and for at least three months after your last dose of Paclitaxel Protein-Bound Particles for Injectable Suspension (albumin-bound).

• are breastfeeding or plan to breastfeed. Do not breastfeed during your treatment and for two weeks after your last dose of Paclitaxel Protein-Bound Particles for Injectable Suspension (albumin-bound).

Tell your healthcare provider about all the medicines you take, including prescription and over-the-counter medicines, vitamins, and herbal supplements.

Know the medicines you take. Keep a list to show your healthcare provider and pharmacist when you get a new medicine.

How will I receive Paclitaxel Protein-Bound Particles for Injectable Suspension (albumin-bound)?

- Your healthcare provider will prescribe Paclitaxel Protein-Bound Particles for Injectable Suspension (albumin-bound) in an amount that is right for you.
- Your healthcare provider may give you certain medicines to help prevent allergic reactions if you have had an allergic reaction to protein bound paclitaxel in the past.
- Paclitaxel Protein-Bound Particles for Injectable Suspension (albumin-bound) will be given to you by intravenous (IV) infusion over 30 minutes into your vein.
- Your healthcare provider should do blood tests regularly during treatment with Paclitaxel Protein-Bound Particles for Injectable Suspension (albumin-bound).
- Your healthcare provider may stop your treatment, delay your treatment, or change your dose of Paclitaxel Protein-Bound Particles for Injectable Suspension (albumin-bound) if you have certain side effects.

What are the possible side effects of Paclitaxel Protein-Bound Particles for Injectable Suspension (albumin-bound)?

Paclitaxel Protein-Bound Particles for Injectable Suspension (albumin-bound) may cause serious side effects, including:

- severe decreased blood cell counts. Protein bound paclitaxel can cause a severe decrease in neutrophils, a type of white blood cell which helps fight infections, and blood cells called platelets which help to clot blood. Your healthcare provider will check your blood cell count during your treatment with Paclitaxel Protein-Bound Particles for Injectable Suspension (albumin-bound).
- severe nerve problems (neuropathy). Nerve problems are common with Paclitaxel Protein-Bound Particles for Injectable Suspension (albumin bound) but can also sometimes be severe. Tell your healthcare provider if you have numbness, tingling, pain, or weakness in your hands or feet.
- severe infection (sepsis). Infections can be severe and life-threatening in people who receive protein bound paclitaxel. Tell your healthcare provider right away if you have a fever (temperature greater than 100.4° F) or develop signs of infection.
- lung or breathing problems. If you receive protein bound paclitaxel, lung or breathing problems may be severe and can lead to death. Tell your healthcare provider right away if you suddenly get a dry cough that will not go away or shortness of breath.
- severe allergic reactions. Severe allergic reactions are medical emergencies that can happen in people who receive protein bound paclitaxel and can lead to death. You may have an increased risk of having an allergic reaction to Paclitaxel Protein-Bound Particles for Injectable Suspension (albumin-bound) if you are allergic to protein bound paclitaxel and other taxane medicines. Your healthcare provider will monitor you closely for allergic reactions during your infusion of Paclitaxel Protein-Bound Particles for Injectable Suspension (albumin-bound). Tell your healthcare provider right away if you get any of these signs of a serious allergic reaction: trouble breathing, sudden swelling of your face, lips, tongue, throat, or trouble swallowing, hives (raised bumps), rash, or redness all over your body.

The most common side effects of protein bound paclitaxel in people with breast cancer include:

- hair loss
- tiredness or weakness
- changes in your liver function tests
- nausea
- infections
- diarrhea

- decreased white blood cell count
- abnormal heartbeat
- joint and muscle pain
- low red blood cell count (anemia). Red blood cells carry oxygen to your body tissues. Tell your healthcare provider if you feel weak, tired, or short of breath.

The most common side effects of protein bound paclitaxel in people with non-small cell lung cancer include:

- low red blood cell count (anemia)
- decreased platelet cell count
- tiredness/weakness

- decreased white blood cell count
- hair loss
- nausea

The most common side effects of protein bound paclitaxel in people with pancreatic cancer include:

- decreased white blood cell count
- hair loss
- infections
- vomiting
- rash

- tiredness/weakness
- nausea
- swelling in the hands or feet
- fever
- decreased appetite
- signs of dehydration including thirst, dry mouth, dark yellow urine, decreased urine, headache, or muscle cramps

Tell your healthcare provider if you have vomiting, diarrhea, or signs of dehydration that does not go away.

Paclitaxel Protein-Bound Particles for Injectable Suspension (albumin-bound) may cause fertility problems in males and females, which may affect your ability to have a child. Talk to your healthcare provider if this is a concern for you. These are not all of the possible side effects of Paclitaxel Protein-Bound Particles for Injectable Suspension (albumin-bound).

Call your doctor for medical advice about side effects. You may report side effects to FDA at 1-800-FDA-1088.

General information about the safe and effective use of Paclitaxel Protein-Bound Particles for Injectable Suspension (albumin-bound).
Medicines are sometimes prescribed for purposes other than those listed in a Patient Information leaflet. You can ask your healthcare provider or pharmacist for information about Paclitaxel Protein-Bound Particles for Injectable Suspension (albumin-bound) that is written for health professionals.

What are the ingredients in Paclitaxel Protein-Bound Particles for Injectable Suspension (albumin-bound)?
Active ingredient: paclitaxel
Inactive ingredients: human albumin (containing sodium caprylate and sodium acetyltryptophanate), sodium chloride.

Manufactured By: Pharmachemie B.V., Haarlem, The Netherlands

Manufactured For: Teva Pharmaceuticals, Parsippany, NJ 07054

For more information, call Teva at 1-888-838-2872.

This Patient Information has been approved by the U.S. Food and Drug Administration. Iss. 11/2023

PACKAGE LABEL.PRINCIPAL DISPLAY PANEL

NDC 0480-3290-01

Read all sides of carton.

Paclitaxel Protein-Bound Particles for Injectable Suspension (albumin-bound)

100 mg/vial

For Intravenous Infusion

Warning: Hazardous Drug

Functional properties differ from other paclitaxel products.

DO NOT SUBSTITUTE.

Single-Dose Vial
Discard any unused portion.

Rx only